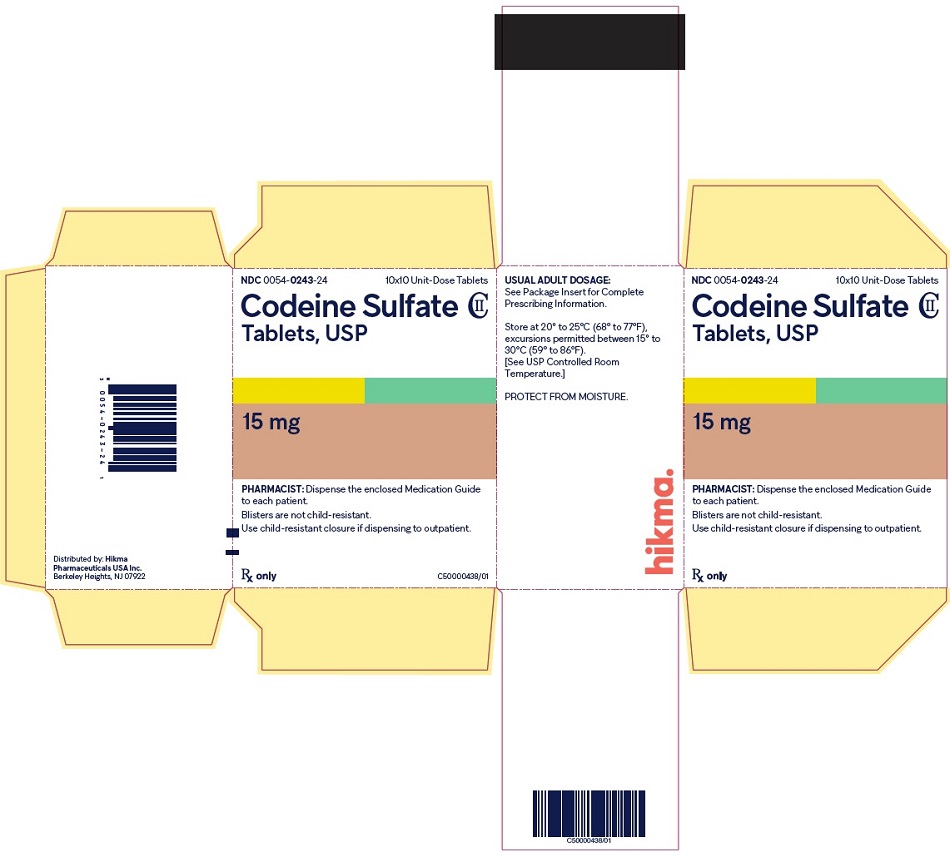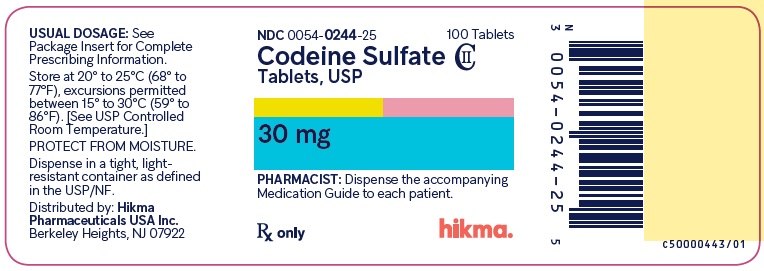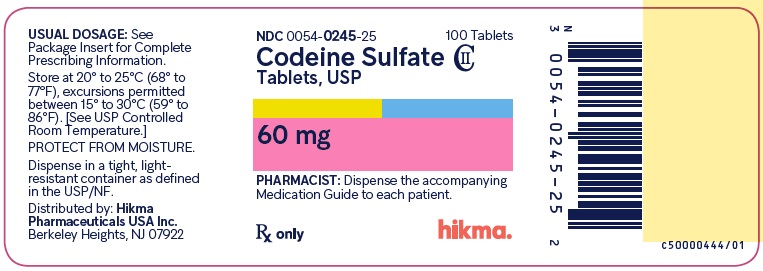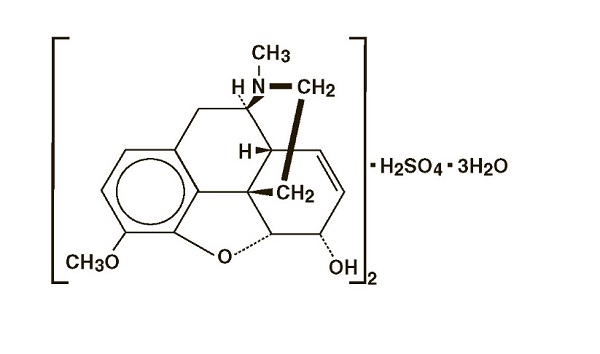 DRUG LABEL: Codeine sulfate
NDC: 0054-0243 | Form: TABLET
Manufacturer: Hikma Pharmaceuticals USA Inc.
Category: prescription | Type: HUMAN PRESCRIPTION DRUG LABEL
Date: 20251222
DEA Schedule: CII

ACTIVE INGREDIENTS: CODEINE SULFATE 15 mg/1 1
INACTIVE INGREDIENTS: MICROCRYSTALLINE CELLULOSE; SILICON DIOXIDE; STARCH, CORN; STEARIC ACID

HIGHLIGHTS OF PRESCRIBING INFORMATION

These highlights do not include all the information needed to use CODEINE SULFATE TABLETS safely and effectively. See full prescribing information for CODEINE SULFATE TABLETS.
CODEINE SULFATE tablets, for oral use CII
Initial U.S. Approval: 1950

RECENT MAJOR CHANGES

Boxed Warning | 12/2025
Indications and Usage (1) | 12/2025
Dosage and Administration (2.2, 2.5) | 12/2025
Warnings and Precautions (5.1, 5.2, 5.3, 5.14, 5.16) | 12/2025

WARNING: SERIOUS AND LIFE-THREATENING RISKS FROM USE OF CODEINE SULFATE TABLETS

See full prescribing information for complete boxed warning.

- Codeine Sulfate Tablets exposes users to risks of addiction, abuse, and misuse, which can lead to overdose and death. Assess patient’s risk before prescribing and reassess regularly for these behaviors and conditions. (5.1)
- Serious, life-threatening, or fatal respiratory depression may occur. Monitor closely, especially upon initiation or following a dosage increase. To reduce the risk of respiratory depression, proper dosing and titration of Codeine Sulfate Tablets are essential. (5.2)
- Accidental ingestion of Codeine Sulfate Tablets, especially by children, can result in a fatal overdose of codeine. (5.2)
- Concomitant use of opioids with benzodiazepines or other central nervous system (CNS) depressants, including alcohol, may result in profound sedation, respiratory depression, coma, and death. Reserve concomitant prescribing for use in patients for whom alternative treatment options are inadequate. (5.3, 7)
- Advise pregnant women using opioids for an extended period of time of the risk of Neonatal Opioid Withdrawal Syndrome, which may be life-threatening if not recognized and treated. Ensure that management by neonatology experts will be available at delivery. (5.4)
- Healthcare providers are strongly encouraged to complete a REMS-compliant education program and to counsel patients and caregivers on serious risks, safe use, and the importance of reading the Medication Guide with each prescription. (5.5)
- Life-threatening respiratory depression and death have occurred in children who received codeine; most cases followed tonsillectomy and/or adenoidectomy and many of the children had evidence of being an ultra-rapid metabolizer of codeine due to a CYP2D6 polymorphism. (5.6) Codeine Sulfate Tablets are contraindicated in children younger than 12 years of age and in children younger than 18 years of age following tonsillectomy and/or adenoidectomy (4). Avoid the use of Codeine Sulfate Tablets in adolescents 12 to 18 years of age who have other risk factors that may increase their sensitivity to the respiratory depressant effects of codeine.
- The effects of concomitant use or discontinuation of cytochrome P450 3A4 inducers, 3A4 inhibitors, or 2D6 inhibitors with codeine are complex. Use of cytochrome P450 3A4 inducers, 3A4 inhibitors, or 2D6 inhibitors with Codeine Sulfate Tablets requires careful consideration of the effects on the parent drug, codeine, and the active metabolite, morphine. (5.7, 7)

1 INDICATIONS AND USAGE

Codeine Sulfate Tablets are an opioid agonist, indicated for the management of mild to moderate pain, where treatment with an opioid is appropriate and for which alternative treatments are inadequate. (1)

Limitations of Use

- Because of the risks of addiction, abuse, misuse, overdose, and death, which can occur at any dosage or duration and persist over the course of therapy, reserve opioid analgesics, including Codeine Sulfate Tablets, for use in patients for whom alternative treatment options are ineffective, not tolerated, or would be otherwise inadequate to provide sufficient management of pain. (1, 5.1)

2 DOSAGE AND ADMINISTRATION

- Codeine Sulfate Tablets should be prescribed only by healthcare professionals who are knowledgeable about the use of opioids and how to mitigate the associated risks. (2.1)
- Use the lowest effective dosage for the shortest duration of time consistent with individual patient treatment goals. Reserve titration to higher doses of Codeine Sulfate Tablets for patients in whom lower doses are insufficiently effective and in whom the expected benefits of using a higher dose opioid clearly outweigh the substantial risks. (2.1, 5)
- Many acute pain conditions (e.g., the pain that occurs with a number of surgical procedures or acute musculoskeletal injuries) require no more than a few days of an opioid analgesic. Clinical guidelines on opioid prescribing for some acute pain conditions are available. (2.1)
- Initiate the dosing regimen for each patient individually, taking into account the patient’s underlying cause and severity of pain, prior analgesic treatment and response, and risk factors for addiction, abuse, and misuse. (2.1, 5.1)
- Respiratory depression can occur at any time during opioid therapy, especially when initiating and following dosage increases with Codeine Sulfate Tablets. Consider this risk when selecting an initial dose and when making dose adjustments. (2.1, 5.2)
- Discuss opioid overdose reversal agents and options for acquiring them with the patient and/or caregiver, both when initiating and renewing treatment with Codeine Sulfate Tablets, especially if the patient has additional risk factors for overdose, or close contacts at risk for exposure and overdose. (2.2, 5.1, 5.2, 5.3)
- Initiate treatment with 15 to 60 mg every 4 hours as needed for pain, and at the lowest dose necessary to achieve adequate analgesia. Titrate the dose based upon the individual patient’s response to their initial dose of Codeine Sulfate Tablets. (2.3)
- Periodically reassess patients receiving Codeine Sulfate Tablets to evaluate the continued need for opioid analgesics to maintain pain control, for the signs or symptoms of adverse reactions, and for the development of addiction, abuse, or misuse. (2.4)
- Do not rapidly reduce or abruptly discontinue Codeine Sulfate Tablets in a physically-dependent patient because rapid reduction or abrupt discontinuation of opioid analgesics has resulted in serious withdrawal symptoms, uncontrolled pain, and suicide. (2.5, 5.16)

3 DOSAGE FORMS AND STRENGTHS

Tablets: 15 mg, 30 mg, and 60 mg (3)

4 CONTRAINDICATIONS

- Children younger than 12 years of age.
- Postoperative management in children younger than 18 years of age following tonsillectomy and/or adenoidectomy. (4)
- Significant respiratory depression. (4)
- Acute or severe bronchial asthma in an unmonitored setting or in absence of resuscitative equipment. (4)
- Concurrent use of monoamine oxidase inhibitors (MAOIs) or use of MAOIs within the last 14 days. (4)
- Known or suspected gastrointestinal obstruction, including paralytic ileus. (4)
- Hypersensitivity to codeine. (4)

5 WARNINGS AND PRECAUTIONS

- Opioid-Induced Hyperalgesia and Allodynia: Opioid-Induced Hyperalgesia (OIH) occurs when an opioid analgesic paradoxically causes an increase in pain, or an increase in sensitivity to pain. If OIH is suspected, carefully consider appropriately decreasing the dose of the current opioid analgesic, or opioid rotation. (5.8)
- Life-Threatening Respiratory Depression in Patients with Chronic Pulmonary Disease or in Elderly, Cachectic, or Debilitated Patients: Regularly evaluate closely, particularly during initiation and titration. (5.9)
- Adrenal Insufficiency: If diagnosed, treat with physiologic replacement of corticosteroids, and wean patient off of the opioid. (5.11)
- Severe Hypotension: Regularly evaluate during dosage initiation and titration. Avoid use of Codeine Sulfate Tablets in patients with circulatory shock. (5.12)
- Risks of Use in Patients with Increased Intracranial Pressure, Brain Tumors, Head Injury, or Impaired Consciousness: Monitor for sedation and respiratory depression. Avoid use of Codeine Sulfate Tablets in patients with impaired consciousness or coma. (5.13)

6 ADVERSE REACTIONS

The most common adverse reactions include: drowsiness, lightheadedness, dizziness, sedation, shortness of breath, nausea, vomiting, and sweating. (6)

To report SUSPECTED ADVERSE REACTIONS, contact Hikma Pharmaceuticals USA Inc. at 1-800-962-8364 or FDA at 1-800-FDA-1088 or www.fda.gov/medwatch.

7 DRUG INTERACTIONS

- Serotonergic Drugs: Concomitant use may result in serotonin syndrome. Discontinue codeine sulfate if serotonin syndrome is suspected. (7)
- Mixed Agonist/Antagonist and Partial Agonist Opioid Analgesics: Avoid use with Codeine Sulfate Tablets because they may reduce analgesic effect of Codeine Sulfate Tablets or precipitate withdrawal symptoms. (7)

8 USE IN SPECIFIC POPULATIONS

- Pregnancy: May cause fetal harm. (8.1)
- Lactation: Breastfeeding not recommended. (8.2)

FULL PRESCRIBING INFORMATION

WARNING: SERIOUS AND LIFE-THREATENING RISKS FROM USE OF CODEINE SULFATE TABLETS

Addiction, Abuse, and Misuse

Because the use of Codeine Sulfate Tablets exposes patients and other users to the risks of opioid addiction, abuse, and misuse, which can lead to overdose and death, assess each patient’s risk prior to prescribing and reassess all patients regularly for the development of these behaviors and conditions [see Warnings and Precautions (5.1), Dosage and Administration (2.1)].

Life-Threatening Respiratory Depression

Serious, life-threatening, or fatal respiratory depression may occur with use of Codeine Sulfate Tablets, especially during initiation or following a dosage increase. To reduce the risk of respiratory depression, proper dosing and titration of Codeine Sulfate Tablets are essential [see Warnings and Precautions (5.2)].

Accidental Ingestion

Accidental ingestion of even one dose of Codeine Sulfate Tablets, especially by children, can result in a fatal overdose of codeine [see Warnings and Precautions (5.2)].

Risks From Concomitant Use With Benzodiazepines Or Other CNS Depressants

Concomitant use of opioids with benzodiazepines or other central nervous system (CNS) depressants, including alcohol, may result in profound sedation, respiratory depression, coma, and death. Reserve concomitant prescribing of Codeine Sulfate Tablets and benzodiazepines or other CNS depressants for use in patients for whom alternative treatment options are inadequate [see Warnings and Precautions (5.3), Drug Interactions (7)].

Neonatal Opioid Withdrawal Syndrome (NOWS)

Advise pregnant women using opioids for an extended period of time of the risk of Neonatal Opioid Withdrawal Syndrome, which may be life-threatening if not recognized and treated. Ensure that management by neonatology experts will be available at delivery. [see Warnings and Precautions (5.4)].

Opioid Analgesic Risk Evaluation and Mitigation Strategy (REMS)

Healthcare providers are strongly encouraged to complete a REMS-compliant education program and to counsel patients and caregivers on serious risks, safe use, and the importance of reading the Medication Guide with each prescription [see Warnings and Precautions (5.5)].

Ultra-Rapid Metabolism of Codeine and Other Risk Factors for Life-Threatening Respiratory Depression in Children

Life-threatening respiratory depression and death have occurred in children who received codeine. Most of the reported cases occurred following tonsillectomy and/or adenoidectomy, and many of the children had evidence of being an ultra-rapid metabolizer of codeine due to a CYP2D6 polymorphism [see Warnings and Precautions (5.6)]. Codeine Sulfate Tablets are contraindicated in children younger than 12 years of age and in children younger than 18 years of age following tonsillectomy and/or adenoidectomy [see Contraindications (4)]. Avoid the use of Codeine Sulfate Tablets in adolescents 12 to 18 years of age who have other risk factors that may increase their sensitivity to the respiratory depressant effects of codeine.

Interactions with Drugs Affecting Cytochrome P450 Isoenzymes

The effects of concomitant use or discontinuation of cytochrome P450 3A4 inducers, 3A4 inhibitors, or 2D6 inhibitors with codeine are complex. Use of cytochrome P450 3A4 inducers, 3A4 inhibitors, or 2D6 inhibitors with Codeine Sulfate Tablets requires careful consideration of the effects on the parent drug, codeine, and the active metabolite, morphine. [See Warnings and Precautions (5.7), Drug Interactions (7)].

1 INDICATIONS AND USAGE

Codeine Sulfate Tablets are indicated for the management of mild to moderate pain, where treatment with an opioid is appropriate and for which alternative treatments are inadequate.

Limitations of Use:

- Because of the risks of addiction, abuse, misuse, overdose, and death, which can occur at any dosage or duration and persist over the course of therapy [see Warnings and Precautions (5.1)], reserve opioid analgesics, including Codeine Sulfate Tablets, for use in patients for whom alternative treatment options are ineffective, not tolerated, or would be otherwise inadequate to provide sufficient management of pain.

2 DOSAGE AND ADMINISTRATION

2.1 Important Dosage and Administration Instructions

- Codeine Sulfate Tablets should be prescribed only by healthcare professionals who are knowledgeable about the use of opioids and how to mitigate the associated risks.
- Use the lowest effective dosage for the shortest duration of time consistent with individual patient treatment goals [see Warnings and Precautions (5)]. Because the risk of overdose increases as opioid doses increase, reserve titration to higher doses of Codeine Sulfate Tablets for patients in whom lower doses are insufficiently effective and in whom the expected benefits of using a higher dose opioid clearly outweigh the substantial risks.
- Many acute pain conditions (e.g., the pain that occurs with a number of surgical procedures or acute musculoskeletal injuries) require no more than a few days of an opioid analgesic. Clinical guidelines on opioid prescribing for some acute pain conditions are available.
- There is variability in the opioid analgesic dose and duration needed to adequately manage pain due both to the cause of pain and to individual patient factors. Initiate the dosing regimen for each patient individually, taking into account the patient’s underlying cause and severity of pain, prior analgesic treatment and response, and risk factors for addiction, abuse, and misuse [see Warnings and Precautions (5.1)].
- Respiratory depression can occur at any time during opioid therapy, especially when initiating and following dosage increases with Codeine Sulfate Tablets. Consider this risk when selecting an initial dose and when making dose adjustments [see Warnings and Precautions (5)].

2.2 Patient Access to an Opioid Overdose Reversal Agent for the Emergency Treatment of Opioid Overdose

Inform patients and caregivers about opioid overdose reversal agents (e.g., naloxone, nalmefene). Discuss the importance of having access to an opioid overdose reversal agent, especially if the patient has risk factors for overdose (e.g., concomitant use of CNS depressants, a history of opioid use disorder, or prior opioid overdose) or if there are household members (including children) or other close contacts at risk for accidental ingestion or opioid overdose. The presence of risk factors for overdose should not prevent the management of pain in any patient [see Warnings and Precautions (5.1, 5.2, 5.3)].

Discuss the options for obtaining an opioid overdose reversal agent (e.g., prescription, over-the-counter, or as part of a community-based program) [see Warnings and Precautions (5.2)].

There are important differences among the opioid overdose reversal agents, such as route of administration, product strength, approved patient age range, and pharmacokinetics. Be familiar with these differences, as outlined in the approved labeling for those products, prior to recommending or prescribing such an agent.

2.3 Initial Dosage

Initiating Treatment with Codeine Sulfate Tablets:

Initiate treatment with Codeine Sulfate Tablets in a dosing range of 15 to 60 mg every 4 hours as needed for pain, and at the lowest dose necessary to achieve adequate analgesia. Titrate the dose based upon the individual patient’s response to their initial dose of Codeine Sulfate Tablets. Adult doses of Codeine Sulfate Tablets higher than 60 mg provide no further efficacy but are associated with greater adverse reactions. The maximum 24-hour dose is 360 mg.

Conversion from Other Opioids to Codeine Sulfate Tablets:

There is inter-patient variability in the potency of opioid drugs and opioid formulations. Therefore, a conservative approach is advised when determining the total daily dosage of Codeine Sulfate Tablets. It is safer to underestimate a patient’s 24-hour Codeine Sulfate Tablets dosage than to overestimate the 24-hour Codeine Sulfate Tablets dosage and manage an adverse reaction due to overdose.

2.4 Titration and Maintenance of Therapy

Individually titrate Codeine Sulfate Tablets to a dose that provides adequate analgesia and minimizes adverse reactions. Continually reevaluate patients receiving codeine sulfate to assess the maintenance of pain control, signs and symptoms of opioid withdrawal, and other adverse reactions as well as to reassess for the development of addiction, abuse, or misuse [see Warnings and Precautions (5.1, 5.16)]. Frequent communication is important among the prescriber, other members of the healthcare team, the patient, and the caregiver/family during periods of changing analgesic requirements, including initial titration.

If the level of pain increases after dosage stabilization, attempt to identify the source of increased pain before increasing the Codeine Sulfate Tablets dosage. If after increasing the dosage, unacceptable opioid-related adverse reactions are observed (including an increase in pain after a dosage increase), consider reducing the dosage [see Warnings and Precautions (5)]. Adjust the dosage to obtain an appropriate balance between management of pain and opioid-related adverse reactions.

2.5 Safe Reduction or Discontinuation of Codeine Sulfate Tablets

Do not rapidly reduce or abruptly discontinue Codeine Sulfate Tablets in patients who may be physically dependent on opioids. Rapid reduction or abrupt discontinuation of opioid analgesics in patients who are physically dependent on opioids has resulted in serious withdrawal symptoms, uncontrolled pain, and suicide. Rapid reduction or abrupt discontinuation has also been associated with attempts to find other sources of opioid analgesics, which may be confused with drug-seeking for abuse. Patients may also attempt to treat their pain or withdrawal symptoms with illicit opioids, such as heroin, and other substances.

When a decision has been made to decrease the dose or discontinue therapy in an opioid-dependent patient taking Codeine Sulfate Tablets, there are a variety of factors that should be considered, including the total daily dose of opioid (including Codeine Sulfate Tablets) the patient has been taking, the duration of treatment, the type of pain being treated, and the physical and psychological attributes of the patient. It is important to ensure ongoing care of the patient and to agree on an appropriate tapering schedule and follow-up plan so that patient and provider goals and expectations are clear and realistic. When opioid analgesics are being discontinued due to a suspected substance use disorder, evaluate and treat the patient, or refer for evaluation and treatment of the substance use disorder. Treatment should include evidence-based approaches, such as medication assisted treatment of opioid use disorder. Complex patients with co-morbid pain and substance use disorders may benefit from referral to a specialist.

There are no standard opioid tapering schedules that are suitable for all patients. Good clinical practice dictates a patient-specific plan to taper the dose of the opioid gradually. For patients on Codeine Sulfate Tablets who are physically opioid-dependent, initiate the taper by a small enough increment (e.g., no greater than 10% to 25% of the total daily dose) to avoid withdrawal symptoms, and proceed with dose-lowering at an interval of every 2 to 4 weeks. Patients who have been taking opioids for briefer periods of time may tolerate a more rapid taper.

It may be necessary to provide the patient with lower dosage strengths to accomplish a successful taper. Reassess the patient frequently to manage pain and withdrawal symptoms, should they emerge. Common withdrawal symptoms include restlessness, lacrimation, rhinorrhea, yawning, perspiration, chills, myalgia, and mydriasis. Other signs and symptoms also may develop, including irritability, anxiety, backache, joint pain, weakness, abdominal cramps, insomnia, nausea, anorexia, vomiting, diarrhea, or increased blood pressure, respiratory rate, or heart rate. If withdrawal symptoms arise, it may be necessary to pause the taper for a period of time or raise the dose of the opioid analgesic to the previous dose, and then proceed with a slower taper. In addition, evaluate patients for any changes in mood, emergence of suicidal thoughts, or use of other substances.

When managing patients taking opioid analgesics, particularly those who have been treated for an extended period of time and/or with high doses for chronic pain, ensure that a multimodal approach to pain management, including mental health support (if needed), is in place prior to initiating an opioid analgesic taper. A multimodal approach to pain management may optimize the treatment of chronic pain, as well as assist with the successful tapering of the opioid analgesic [see Warnings and Precautions (5.16), Drug Abuse and Dependence (9.3)].

3 DOSAGE FORMS AND STRENGTHS

Each 15 mg tablet for oral administration contains 15 mg of codeine sulfate, USP. It is a white to off-white biconvex tablet with “15” debossed on the scored side and “54 613” debossed on the other side.

Each 30 mg tablet for oral administration contains 30 mg of codeine sulfate, USP. It is a white to off-white biconvex tablet with “30” debossed on the scored side and “54 783” debossed on the other side.

Each 60 mg tablet for oral administration contains 60 mg of codeine sulfate, USP. It is a white to off-white biconvex tablet with “60” debossed on the scored side and “54 412” debossed on the other side.

4 CONTRAINDICATIONS

Codeine Sulfate Tablets are contraindicated for:

- All children younger than 12 years of age [see Warnings and Precautions (5.6)].
- Post-operative management in children younger than 18 years of age following tonsillectomy and/or adenoidectomy [see Warnings and Precautions (5.6)].

Codeine Sulfate Tablets are also contraindicated in patients with:

- Significant respiratory depression [see Warnings and Precautions (5.2)].
- Acute or severe bronchial asthma in an unmonitored setting or in the absence of resuscitative equipment [see Warnings and Precautions (5.9)].
- Concurrent use of monoamine oxidase inhibitors (MAOIs) or use of MAOIs within the last 14 days [see Warnings and Precautions (5.10), Drug Interactions (7)].
- Known or suspected gastrointestinal obstruction, including paralytic ileus [see Warnings and Precautions (5.14)].
- Hypersensitivity to codeine (e.g., anaphylaxis) [see Adverse Reactions (6)].

5 WARNINGS AND PRECAUTIONS

5.1 Addiction, Abuse, and Misuse

Codeine Sulfate Tablets contain codeine, a Schedule II controlled substance. As an opioid, Codeine Sulfate Tablets exposes users to the risks of addiction, abuse, and misuse [see Drug Abuse and Dependence (9)].

Although the risk of addiction in any individual is unknown, it can occur in patients appropriately prescribed Codeine Sulfate Tablets. Addiction can occur at recommended dosages and if the drug is misused or abused. The risk of opioid-related overdose or overdose-related death is increased with higher opioid doses, and this risk persists over the course of therapy. In postmarketing studies, addiction, abuse, misuse, and fatal and non-fatal opioid overdose were observed in patients with long-term opioid use [see Adverse Reactions (6)].

Assess each patient’s risk for opioid addiction, abuse, or misuse prior to prescribing Codeine Sulfate Tablets, and reassess all patients receiving Codeine Sulfate Tablets for the development of these behaviors and conditions. Risks are increased in patients with a personal or family history of substance abuse (including drug or alcohol abuse or addiction) or mental illness (e.g., major depression). The potential for these risks should not, however, prevent the proper management of pain in any given patient. Patients at increased risk may be prescribed opioids such as Codeine Sulfate Tablets, but use in such patients necessitates intensive counseling about the risks and proper use of Codeine Sulfate Tablets along with frequent reevaluation for signs of addiction, abuse, and misuse. Consider recommending or prescribing an opioid overdose reversal agent [see Dosage and Administration (2.2), Warnings and Precautions (5.2)].

Opioids are sought for nonmedical use and are subject to diversion from legitimate prescribed use. Consider these risks when prescribing or dispensing Codeine Sulfate Tablets. Strategies to reduce these risks include prescribing the drug in the smallest appropriate quantity and advising the patient on careful storage of the drug during the course of treatment and proper disposal of unused drug. Contact local state professional licensing board or state-controlled substances authority for information on how to prevent and detect abuse or diversion of this product.

5.2 Life-Threatening Respiratory Depression

Serious, life-threatening, or fatal respiratory depression has been reported with the use of opioids, even when used as recommended. Respiratory depression, if not immediately recognized and treated, may lead to respiratory arrest and death. Management of respiratory depression may include close observation, supportive measures, and use of opioid overdose reversal agents, depending on the patient’s clinical status [see Overdosage (10)]. Carbon dioxide (CO2) retention from opioid-induced respiratory depression can exacerbate the sedating effects of opioids.

While serious, life-threatening, or fatal respiratory depression can occur at any time during the use of Codeine Sulfate Tablets, the risk is greatest during the initiation of therapy or following a dosage increase.

To reduce the risk of respiratory depression, proper dosing and titration of Codeine Sulfate Tablets are essential [see Dosage and Administration (2.3, 2.4)]. Overestimating the Codeine Sulfate Tablets dosage when converting patients from another opioid product can result in a fatal overdose with the first dose.

Accidental ingestion of even one dose of Codeine Sulfate Tablets, especially by children, can result in respiratory depression and death due to an overdose of codeine.

Educate patients and caregivers on how to recognize respiratory depression and emphasize the importance of calling 911 or getting emergency medical help right away in the event of a known or suspected overdose.

Opioids can cause sleep-related breathing disorders including central sleep apnea (CSA) and sleep-related hypoxemia. Opioid use increases the risk of CSA in a dose-dependent fashion. In patients who present with CSA, consider decreasing the opioid dosage using best practices for opioid taper [see Dosage and Administration (2.4)].

Patient Access to an Opioid Overdose Reversal Agent for the Emergency Treatment of Opioid Overdose:

Inform patients and caregivers about opioid overdose reversal agents (e.g., naloxone, nalmefene). Discuss the importance of having access to an opioid overdose reversal agent, especially if the patient has risk factors for overdose (e.g., concomitant use of CNS depressants, a history of opioid use disorder, or prior opioid overdose) or if there are household members (including children) or other close contacts at risk for accidental ingestion or opioid overdose. The presence of risk factors for overdose should not prevent the management of pain in any patient [see Warnings and Precautions (5.1, 5.3)].

Discuss the options for obtaining an opioid overdose reversal agent (e.g., prescription, over-the-counter, or as part of a community-based program).

There are important differences among the opioid overdose reversal agents, such as route of administration, product strength, approved patient age range, and pharmacokinetics. Be familiar with these differences, as outlined in the approved labeling for those products, prior to recommending or prescribing such an agent.

Educate patients and caregivers on how to recognize respiratory depression, and how to use an opioid overdose reversal agent for the emergency treatment of opioid overdose. Emphasize the importance of calling 911 or getting emergency medical help, even if an opioid overdose reversal agent is administered [see Dosage and Administration (2.2), Warnings and Precautions (5.1, 5.3), Overdosage (10)].

5.3 Risks from Concomitant Use with Benzodiazepines or Other CNS Depressants

Profound sedation, respiratory depression, coma, and death may result from the concomitant use of Codeine Sulfate Tablets with benzodiazepines and/or other CNS depressants, including alcohol (e.g., non-benzodiazepine sedatives/hypnotics, anxiolytics, tranquilizers, muscle relaxants, general anesthetics, antipsychotics, gabapentinoids [gabapentin or pregabalin], and other opioids). Because of these risks, reserve concomitant prescribing of these drugs for use in patients for whom alternative treatment options are inadequate.

Observational studies have demonstrated that concomitant use of opioid analgesics and benzodiazepines increases the risk of drug-related mortality compared to use of opioid analgesics alone. Because of similar pharmacological properties, it is reasonable to expect similar risk with the concomitant use of other CNS depressant drugs with opioid analgesics [see Drug Interactions (7)].

If the decision is made to prescribe a benzodiazepine or other CNS depressant concomitantly with an opioid analgesic, prescribe the lowest effective dosages and minimum durations of concomitant use. In patients already receiving an opioid analgesic, prescribe a lower initial dose of the benzodiazepine or other CNS depressant than indicated in the absence of an opioid, and titrate based on clinical response. If an opioid analgesic is initiated in a patient already taking a benzodiazepine or other CNS depressant, prescribe a lower initial dose of the opioid analgesic, and titrate based on clinical response. Inform patients and caregivers of this potential interaction and educate them on the signs and symptoms of respiratory depression (including sedation).

If concomitant use is warranted, consider recommending or prescribing an opioid overdose reversal agent [see Dosage and Administration (2.2), Warnings and Precautions (5.2), Overdosage (10)].

Advise both patients and caregivers about the risks of respiratory depression and sedation when Codeine Sulfate Tablets are used with benzodiazepines or other CNS depressants (including alcohol and illicit drugs). Advise patients not to drive or operate heavy machinery until the effects of concomitant use of the benzodiazepine or other CNS depressant have been determined. Screen patients for risk of substance use disorders, including opioid abuse and misuse, and warn them of the risk for overdose and death associated with the use of additional CNS depressants including alcohol and illicit drugs [see Drug Interactions (7)].

5.4 Neonatal Opioid Withdrawal Syndrome

Use of Codeine Sulfate Tablets for an extended period of time during pregnancy can result in withdrawal in the neonate. Neonatal opioid withdrawal syndrome, unlike opioid withdrawal syndrome in adults, may be life-threatening if not recognized and treated, and requires management according to protocols developed by neonatology experts. Observe newborns for signs of neonatal opioid withdrawal syndrome and manage accordingly. Advise pregnant women using opioids for an extended period of time of the risk of neonatal opioid withdrawal syndrome and ensure that appropriate treatment will be available [see Use in Specific Populations (8.1)].

5.5 Opioid Analgesic Risk Evaluation and Mitigation Strategy (REMS)

To ensure that the benefits of opioid analgesics outweigh the risks of addiction, abuse, and misuse, the Food and Drug Administration (FDA) has required a Risk Evaluation and Mitigation Strategy (REMS) for these products. Under the requirements of the REMS, drug companies with approved opioid analgesic products must make REMS-compliant education programs available to healthcare providers. Healthcare providers are strongly encouraged to do all of the following:

- Complete a REMS-compliant education program offered by an accredited provider of continuing education (CE) or another education program that includes all the elements of the FDA Education Blueprint for Health Care Providers Involved in the Management or Support of Patients with Pain.
- Discuss the safe use, serious risks, and proper storage and disposal of opioid analgesics with patients and/or their caregivers every time these medicines are prescribed. The Patient Counseling Guide (PCG) can be obtained at this link: www.fda.gov/OpioidAnalgesicREMSPCG.
- Emphasize to patients and their caregivers the importance of reading the Medication Guide that they will receive from their pharmacist every time an opioid analgesic is dispensed to them.
- Consider using other tools to improve patient, household, and community safety, such as patient-prescriber agreements that reinforce patient-prescriber responsibilities.

To obtain further information on the opioid analgesic REMS and for a list of accredited REMS CME/CE, call 1-800-503-0784, or log on to www.opioidanalgesicrems.com. The FDA Blueprint can be found at www.fda.gov\OpioidAnalgesicREMSBlueprint.

5.6 Ultra-Rapid Metabolism of Codeine and Other Risk Factors for Life-Threatening Respiratory Depression in Children

Life-threatening respiratory depression and death have occurred in children who received codeine. Codeine is subject to variability in metabolism based upon CYP2D6 genotype (described below), which can lead to an increased exposure to the active metabolite morphine. Based upon post-marketing reports, children younger than 12 years old appear to be more susceptible to the respiratory depressant effects of codeine, particularly if there are risk factors for respiratory depression. For example, many reported cases of death occurred in the post-operative period following tonsillectomy and/or adenoidectomy, and many of the children had evidence of being ultra-rapid metabolizers of codeine. Furthermore, children with obstructive sleep apnea who are treated with codeine for post-tonsillectomy and/or adenoidectomy pain may be particularly sensitive to its respiratory depressant effect. Because of the risk of life-threatening respiratory depression and death:

- Codeine Sulfate Tablets are contraindicated for all children younger than 12 years of age [see Contraindications (4)].
- Codeine Sulfate Tablets are contraindicated for post-operative management in pediatric patients younger than 18 years of age following tonsillectomy and/or adenoidectomy [see Contraindications (4)].
- Avoid the use of Codeine Sulfate Tablets in adolescents 12 to 18 years of age who have other risk factors that may increase their sensitivity to the respiratory depressant effects of codeine unless the benefits outweigh the risks. Risk factors include conditions associated with hypoventilation, such as postoperative status, obstructive sleep apnea, obesity, severe pulmonary disease, neuromuscular disease, and concomitant use of other medications that cause respiratory depression. [see Warnings and Precautions (5.6)]
- As with adults, when prescribing codeine for adolescents, healthcare providers should choose the lowest effective dose for the shortest period of time and inform patients and caregivers about these risks and the signs of morphine overdose [see Use in Specific Populations (8.4), Overdosage (10)].

Nursing Mothers:

At least one death was reported in a nursing infant who was exposed to high levels of morphine in breast milk because the mother was an ultra-rapid metabolizer of codeine. Breastfeeding is not recommended during treatment with Codeine Sulfate Tablets [see Use in Specific Populations (8.2)].

CYP2D6 Genetic Variability: Ultra-Rapid Metabolizers:

Some individuals may be ultra-rapid metabolizers because of a specific CYP2D6 genotype (e.g., gene duplications denoted as *1/*1xN or *1/*2xN). The prevalence of this CYP2D6 phenotype varies widely and has been estimated at 1 to 10% for Whites (European, North American), 3 to 4% for Blacks (African Americans), 1 to 2% for East Asians (Chinese, Japanese, Korean), and may be greater than 10% in certain racial/ethnic groups (i.e., Oceanian, Northern African, Middle Eastern, Ashkenazi Jews, Puerto Rican).

These individuals convert codeine into its active metabolite, morphine, more rapidly and completely than other people. This rapid conversion results in higher than expected serum morphine levels. Even at labeled dosage regimens, individuals who are ultra-rapid metabolizers may have life-threatening or fatal respiratory depression or experience signs of overdose (such as extreme sleepiness, confusion, or shallow breathing) [see Overdosage (10)]. Therefore, individuals who are ultra-rapid metabolizers should not use Codeine Sulfate Tablets.

5.7 Risks of Interactions with Drugs Affecting Cytochrome P450 Isoenzymes

The effects of concomitant use or discontinuation of cytochrome P450 3A4 inducers, 3A4 inhibitors, or 2D6 inhibitors with codeine are complex. Use of cytochrome P450 3A4 inducers, 3A4 inhibitors, or 2D6 inhibitors with Codeine Sulfate Tablets requires careful consideration of the effects on the parent drug, codeine, and the active metabolite, morphine.

Cytochrome P450 3A4 Interaction:

The concomitant use of Codeine Sulfate Tablets with all cytochrome P450 3A4 inhibitors, such as macrolide antibiotics (e.g., erythromycin), azole-antifungal agents (e.g., ketoconazole), and protease inhibitors (e.g., ritonavir) or discontinuation of a cytochrome P450 3A4 inducer such as rifampin, carbamazepine, and phenytoin, may result in an increase in codeine plasma concentrations with subsequently greater metabolism by cytochrome P450 2D6, resulting in greater morphine levels, which could increase or prolong adverse reactions and may cause potentially fatal respiratory depression.

The concomitant use of Codeine Sulfate Tablets with all cytochrome P450 3A4 inducers or discontinuation of a cytochrome P450 3A4 inhibitor may result in lower codeine levels, greater norcodeine levels, and less metabolism via 2D6 with resultant lower morphine levels. This may be associated with a decrease in efficacy, and in some patients, may result in signs and symptoms of opioid withdrawal. Regularly evaluate patients receiving Codeine Sulfate Tablets and any CYP3A4 inhibitor or inducer for signs and symptoms that may reflect opioid toxicity and opioid withdrawal when Codeine Sulfate Tablets are used in conjunction with inhibitors and inducers of CYP3A4.

If concomitant use of a CYP3A4 inhibitor is necessary or if a CYP3A4 inducer is discontinued, consider dosage reduction of Codeine Sulfate Tablets until stable drug effects are achieved. Evaluate patients at frequent intervals for respiratory depression and sedation.

If concomitant use of a CYP3A4 inducer is necessary or if a CYP3A4 inhibitor is discontinued, consider increasing the Codeine Sulfate Tablets dosage until stable drug effects are achieved. Evaluate patients at frequent intervals for signs of opioid withdrawal [Drug Interactions (7)].

Risks of Concomitant Use or Discontinuation of Cytochrome P450 2D6 Inhibitors:

The concomitant use of Codeine Sulfate Tablets with all cytochrome P450 2D6 inhibitors (e.g., amiodarone, quinidine) may result in an increase in codeine plasma concentrations and a decrease in active metabolite morphine plasma concentration which could result in an analgesic efficacy reduction or symptoms of opioid withdrawal.

Discontinuation of a concomitantly used cytochrome P450 2D6 inhibitor may result in a decrease in codeine plasma concentration and an increase in active metabolite morphine plasma concentration which could increase or prolong adverse reactions and may cause potentially fatal respiratory depression.

Regularly evaluate patients receiving Codeine Sulfate Tablets and any CYP2D6 inhibitor for signs and symptoms that may reflect opioid toxicity and opioid withdrawal when Codeine Sulfate Tablets are used in conjunction with inhibitors of CYP2D6.

If concomitant use with a CYP2D6 inhibitor is necessary, evaluate the patient at frequent intervals for signs of reduced efficacy or opioid withdrawal and consider increasing the Codeine Sulfate Tablets dosage. After stopping use of a CYP2D6 inhibitor, consider reducing the Codeine Sulfate Tablets dosage and evaluate the patient at frequent intervals for signs and symptoms of respiratory depression or sedation [see Drug Interactions (7)].

5.8 Opioid-Induced Hyperalgesia and Allodynia

Opioid-Induced Hyperalgesia (OIH) occurs when an opioid analgesic paradoxically causes an increase in pain, or an increase in sensitivity to pain. This condition differs from tolerance, which is the need for increasing doses of opioids to maintain a defined effect [see Drug Abuse and Dependence (9.3)]. Symptoms of OIH include (but may not be limited to) increased levels of pain upon opioid dosage increase, decreased levels of pain upon opioid dosage decrease, or pain from ordinarily non-painful stimuli (allodynia). These symptoms may suggest OIH only if there is no evidence of underlying disease progression, opioid tolerance, opioid withdrawal, or addictive behavior.

Cases of OIH have been reported, both with short-term and longer-term use of opioid analgesics. Though the mechanism of OIH is not fully understood, multiple biochemical pathways have been implicated. Medical literature suggests a strong biologic plausibility between opioid analgesics and OIH and allodynia. If a patient is suspected to be experiencing OIH, carefully consider appropriately decreasing the dose of the current opioid analgesic, or opioid rotation (safely switching the patient to a different opioid moiety) [see Dosage and Administration (2.5), Warnings and Precautions (5.16].

5.9 Life-Threatening Respiratory Depression in Patients with Chronic Pulmonary Disease or in Elderly, Cachectic, or Debilitated Patients

The use of Codeine Sulfate Tablets in patients with acute or severe bronchial asthma in an unmonitored setting or in the absence of resuscitative equipment is contraindicated.

Patients with Chronic Pulmonary Disease:

Codeine Sulfate Tablets-treated patients with significant chronic obstructive pulmonary disease or cor pulmonale, and those with a substantially decreased respiratory reserve, hypoxia, hypercapnia, or pre-existing respiratory depression are at increased risk of decreased respiratory drive including apnea, even at recommended dosages of Codeine Sulfate Tablets [see Warnings and Precautions (5.2)].

Elderly, Cachectic, or Debilitated Patients:

Life-threatening respiratory depression is more likely to occur in elderly, cachectic, or debilitated patients because they may have altered pharmacokinetics or altered clearance compared to younger, healthier patients [see Warnings and Precautions (5.2)].

Regularly evaluate such patients closely, particularly when initiating and titrating Codeine Sulfate Tablets and when Codeine Sulfate Tablets are given concomitantly with other drugs that depress respiration [see Warnings and Precautions (5.3), Drug Interactions (7)]. Alternatively, consider the use of non-opioid analgesics in these patients.

5.10 Interaction with Monoamine Oxidase Inhibitors

Monoamine oxidase inhibitors (MAOIs) may potentiate the effects of morphine, codeine’s active metabolite, including respiratory depression, coma, and confusion. Codeine Sulfate Tablets should not be used in patients taking MAOIs or within 14 days of stopping such treatment [see Drug Interactions (7)].

5.11 Adrenal Insufficiency

Cases of adrenal insufficiency have been reported with opioid use, more often following greater than one month of use. Presentation of adrenal insufficiency may include non-specific symptoms and signs including nausea, vomiting, anorexia, fatigue, weakness, dizziness, and low blood pressure. If adrenal insufficiency is suspected, confirm the diagnosis with diagnostic testing as soon as possible. If adrenal insufficiency is diagnosed, treat with physiologic replacement doses of corticosteroids. Wean the patient off of the opioid to allow adrenal function to recover and continue corticosteroid treatment until adrenal function recovers. Other opioids may be tried as some cases reported use of a different opioid without recurrence of adrenal insufficiency. The information available does not identify any particular opioids as being more likely to be associated with adrenal insufficiency.

5.12 Severe Hypotension

Codeine Sulfate Tablets may cause severe hypotension including orthostatic hypotension and syncope in ambulatory patients. There is increased risk in patients whose ability to maintain blood pressure has already been compromised by a reduced blood volume or concurrent administration of certain CNS depressant drugs (e.g., phenothiazines or general anesthetics) [see Drug Interactions (7)]. Regularly evaluate these patients for signs of hypotension after initiating or titrating the dosage of Codeine Sulfate Tablets. In patients with circulatory shock, Codeine Sulfate Tablets may cause vasodilation that can further reduce cardiac output and blood pressure. Avoid the use of Codeine Sulfate Tablets in patients with circulatory shock.

5.13 Risks of Use in Patients with Increased Intracranial Pressure, Brain Tumors, Head Injury, or Impaired Consciousness

In patients who may be susceptible to the intracranial effects of CO2 retention (e.g., those with evidence of increased intracranial pressure or brain tumors), Codeine Sulfate Tablets may reduce respiratory drive, and the resultant CO2 retention can further increase intracranial pressure. Monitor such patients for signs of sedation and respiratory depression, particularly when initiating therapy with Codeine Sulfate Tablets.

Opioids may also obscure the clinical course in a patient with a head injury. Avoid the use of Codeine Sulfate Tablets in patients with impaired consciousness or coma.

5.14 Risks of Gastrointestinal Complications

Codeine Sulfate Tablets are contraindicated in patients with known or suspected gastrointestinal obstruction, including paralytic ileus.

The codeine in Codeine Sulfate Tablets may cause spasm of the sphincter of Oddi. Opioids may cause increases in serum amylase. Regularly evaluate patients with biliary tract disease, including pancreatitis, for worsening symptoms.

Cases of opioid-induced esophageal dysfunction (OIED) have been reported in patients taking opioids. The risk of OIED may increase as the dose and/or duration of opioids increases. Regularly evaluate patients for signs and symptoms of OIED (e.g., dysphagia, regurgitation, non-cardiac chest pain) and, if necessary, adjust opioid therapy as clinically appropriate [see Clinical Pharmacology (12.2)].

5.15 Increased Risk of Seizures in Patients with Seizure Disorders

The codeine in Codeine Sulfate Tablets may increase the frequency of seizures in patients with seizure disorders, and may increase the risk of seizures occurring in other clinical settings associated with seizures. Regularly evaluate patients with a history of seizure disorders for worsened seizure control during Codeine Sulfate Tablets therapy.

5.16 Withdrawal

Do not rapidly reduce or abruptly discontinue Codeine Sulfate Tablets in a patient physically dependent on opioids. When discontinuing Codeine Sulfate Tablets in a physically-dependent patient, gradually taper the dosage. Rapid tapering of codeine in a patient physically dependent on opioids may lead to a withdrawal syndrome and return of pain [see Dosage and Administration (2.5), Drug Abuse and Dependence (9.3)].

Additionally, avoid the use of mixed agonist/antagonist (e.g., pentazocine, nalbuphine, and butorphanol) or partial agonist (e.g., buprenorphine) analgesics in patients who are receiving a full opioid agonist analgesic, including Codeine Sulfate Tablets. In these patients, mixed agonist/antagonist and partial agonist analgesics may reduce the analgesic effect and/or precipitate withdrawal symptoms [see Drug Interactions (7)].

5.17 Risks of Driving and Operating Machinery

Codeine Sulfate Tablets may impair the mental or physical abilities needed to perform potentially hazardous activities such as driving a car or operating machinery. Warn patients not to drive or operate dangerous machinery unless they are tolerant to the effects of Codeine Sulfate Tablets and know how they will react to the medication.

6 ADVERSE REACTIONS

The following serious adverse reactions are described, or described in greater detail, in other sections:

- Addiction, Abuse, and Misuse [see Warnings and Precautions (5.1)]
- Life-Threatening Respiratory Depression [see Warnings and Precautions (5.2)]
- Interactions with Benzodiazepines and Other CNS Depressants [see Warnings and Precautions (5.3)]
- Neonatal Opioid Withdrawal Syndrome [see Warnings and Precautions (5.4)]
- Ultra-Rapid Metabolism of Codeine and Other Risk Factors for Life-Threatening Respiratory Depression in Children [see Warnings and Precautions (5.6)]
- Opioid-Induced Hyperalgesia and Allodynia [see Warnings and Precautions (5.8)]
- Adrenal Insufficiency [see Warnings and Precautions (5.11)]
- Severe Hypotension [see Warnings and Precautions (5.12)]
- Gastrointestinal Adverse Reactions [see Warnings and Precautions (5.14)]
- Seizures [see Warnings and Precautions (5.15)]
- Withdrawal [see Warnings and Precautions (5.16)]

The following adverse reactions associated with the use of codeine were identified in clinical studies or postmarketing reports. Because some of these reactions were reported voluntarily from a population of uncertain size, it is not always possible to reliably estimate their frequency or establish a causal relationship to drug exposure.

Serious adverse reactions associated with codeine were respiratory depression and, to a lesser degree, circulatory depression, respiratory arrest, shock, and cardiac arrest.

The most frequently observed adverse reactions with codeine administration included drowsiness, lightheadedness, dizziness, sedation, shortness of breath, nausea, vomiting, sweating, and constipation.

Other adverse reactions included allergic reactions, euphoria, dysphoria, abdominal pain, and pruritis.

Other less frequently observed adverse reactions expected from opioid analgesics, including Codeine Sulfate Tablets, include:

Cardiovascular System: faintness, flushing, hypotension, palpitations, syncope

Digestive System: abdominal cramps, anorexia, diarrhea, dry mouth, gastrointestinal distress, pancreatitis

Nervous System: anxiety, drowsiness, fatigue, headache, insomnia, nervousness, shakiness, somnolence, vertigo, visual disturbances, weakness

Skin and Appendages: rash, sweating, urticaria

Serotonin Syndrome: Cases of serotonin syndrome, a potentially life-threatening condition, have been reported during concomitant use of opioids with serotonergic drugs.

Adrenal Insufficiency: Cases of adrenal insufficiency have been reported with opioid use, more often following greater than one month of use.

Anaphylaxis: Anaphylaxis has been reported with ingredients contained in Codeine Sulfate Tablets.

Androgen Deficiency: Cases of androgen deficiency have occurred with use of opioids for an extended period of time [see Clinical Pharmacology (12.2)].

Hyperalgesia and Allodynia: Cases of hyperalgesia and allodynia have been reported with opioid therapy of any duration [see Warnings and Precautions (5.8)].

Hypoglycemia: Cases of hypoglycemia have been reported in patients taking opioids. Most reports were in patients with at least one predisposing risk factor (e.g., diabetes).

Opioid-induced esophageal dysfunction (OIED): Cases of OIED have been reported in patients taking opioids and may occur more frequently in patients taking higher doses of opioids, and/or in patients taking opioids longer term [see Warnings and Precautions (5.14)].

Adverse Reactions from Observational Studies

A prospective, observational cohort study estimated the risks of addiction, abuse, and misuse in patients initiating long-term use of Schedule II opioid analgesics between 2017 and 2021. Study participants included in one or more analyses had been enrolled in selected insurance plans or health systems for at least one year, were free of at least one outcome at baseline, completed a minimum number of follow-up assessments, and either: 1) filled multiple extended-release/long-acting opioid analgesic prescriptions during a 90-day period (n=978); or 2) filled any Schedule II opioid analgesic prescriptions covering at least 70 of 90 days (n=1,244). Those included also had no dispensing of the qualifying opioids in the previous 6 months.

Over 12 months:

- approximately 1% to 6% of participants across the two cohorts newly met criteria for addiction, as assessed with two validated interview-based measures of moderate-to-severe opioid use disorder based on Diagnostic and Statistical Manual of Mental Disorders, Fifth Edition (DSM-5) criteria, and
- approximately 9% and 22% of participants across the two cohorts newly met criteria for prescription opioid abuse and misuse [defined in Drug Abuse and Dependence (9.2)], respectively, as measured with a validated self-reported instrument.

A retrospective, observational cohort study estimated the risk of opioid-involved overdose or opioid overdose-related death in patients with new long-term use of Schedule II opioid analgesics from 2006 through 2016 (n=220,249). Included patients had been enrolled in either one of two commercial insurance programs, one managed care program, or one Medicaid program for at least 9 months. New long-term use was defined as having Schedule II opioid analgesic prescriptions covering at least 70 days’ supply over the 3 months prior to study entry and none during the preceding 6 months. Patients were excluded if they had an opioid-involved overdose in the 9 months prior to study entry. Overdose was measured using a validated medical code-based algorithm with linkage to the National Death Index database. The 5-year cumulative incidence estimates for opioid-involved overdose or opioid overdose-related death ranged from approximately 1.5% to 4% across study sites, counting only the first event during follow-up. Approximately 17% of first opioid overdoses observed over the entire study period (5-11 years, depending on the study site) were fatal. Higher baseline opioid dose was the strongest and most consistent predictor of opioid-involved overdose or opioid overdose-related death. Study exclusion criteria may have selected patients at lower risk of overdose, and substantial loss to follow-up (approximately 80%) also may have biased estimates.

The risk estimates from the studies described above may not be generalizable to all patients receiving opioid analgesics, such as those with exposures shorter or longer than the duration evaluated in the studies.

7 DRUG INTERACTIONS

Table 1 includes clinically significant drug interactions with Codeine Sulfate Tablets.

Table 1: Clinically Significant Drug Interactions with Codeine Sulfate Tablets
Inhibitors of CYP3A4
Clinical Impact: | The concomitant use of Codeine Sulfate Tablets with CYP3A4 inhibitors, may result in an increase in codeine plasma concentrations with subsequently greater metabolism by cytochrome CYP2D6, resulting in greater morphine levels, which could increase or prolong adverse reactions and may cause potentially fatal respiratory depression, particularly when an inhibitor is added after a stable dose of Codeine Sulfate Tablets is achieved [see Warnings and Precautions (5.7)].; After stopping a CYP3A4 inhibitor, as the effects of the inhibitor decline, it may result in lower codeine levels, greater norcodeine levels, and less metabolism via CYP2D6 with resultant lower morphine levels [see Clinical Pharmacology (12.3)], resulting in decreased opioid efficacy or a withdrawal syndrome in patients who had developed physical dependence to codeine.
Intervention: | If concomitant use of CYP3A4 inhibitor is necessary, consider dosage reduction of Codeine Sulfate Tablets until stable drug effects are achieved. Evaluate patients at frequent intervals for respiratory depression and sedation.; If a CYP3A4 inhibitor is discontinued, consider increasing the Codeine Sulfate Tablets dosage until stable drug effects are achieved. Assess for signs of opioid withdrawal.
Examples: | Macrolide antibiotics (e.g., erythromycin), azole-antifungal agents (e.g. ketoconazole), protease inhibitors (e.g., ritonavir)
CYP3A4 Inducers
Clinical Impact: | The concomitant use of Codeine Sulfate Tablets and CYP3A4 inducers can result in lower codeine levels, greater norcodeine levels, and less metabolism via 2D6 with resultant lower morphine levels [see Clinical Pharmacology (12.3)], resulting in decreased efficacy or onset of a withdrawal syndrome in patients who have developed physical dependence [see Warnings and Precautions (5.7)].; After stopping a CYP3A4 inducer, as the effects of the inducer decline, codeine plasma concentrations may increase with subsequently greater metabolism by cytochrome CYP2D6, resulting in greater morphine levels [see Clinical Pharmacology (12.3)], which could increase or prolong both the therapeutic effects and adverse reactions, and may cause serious respiratory depression.
Intervention: | If concomitant use of a CYP3A4 inducer is necessary, evaluate patients at frequent intervals for reduced efficacy and signs of opioid withdrawal and consider increasing the Codeine Sulfate Tablets dosage as needed.; If a CYP3A4 inducer is discontinued, consider Codeine Sulfate Tablets dosage reduction and evaluate patients at frequent intervals for signs of respiratory depression and sedation.
Examples: | Rifampin, carbamazepine, phenytoin
Inhibitors of CYP2D6
Clinical Impact: | Codeine is metabolized by CYP2D6 to form morphine. The concomitant use of Codeine Sulfate Tablets and CYP2D6 inhibitors can increase the plasma concentration of codeine, but can decrease the plasma concentration of active metabolite morphine, which could result in reduced analgesic efficacy or symptoms of opioid withdrawal, particularly when an inhibitor is added after a stable dose of Codeine Sulfate Tablets is achieved [see Clinical Pharmacology (12.3)].; After stopping a CYP2D6 inhibitor, as the effects of the inhibitor decline, the codeine plasma concentration will decrease but the active metabolite morphine plasma concentration will increase, which could increase or prolong adverse reactions and may cause potentially fatal respiratory depression [see Clinical Pharmacology (12.3)].
Intervention: | If concomitant use with a CYP2D6 inhibitor is necessary, or if a CYP2D6 inhibitor is discontinued after concomitant use, consider dosage adjustment of Codeine Sulfate Tablets and evaluate patients at frequent intervals.; If concomitant use with CYP2D6 inhibitors is necessary, evaluate patients for reduced efficacy or signs and symptoms of opioid withdrawal and consider increasing the dosage of Codeine Sulfate Tablets as needed.; After stopping use of a CYP2D6 inhibitor, consider reducing the dosage of Codeine Sulfate Tablets and evaluate patients at frequent intervals for signs and symptoms of respiratory depression or sedation.
Examples: | Paroxetine, fluoxetine, bupropion, quinidine.
Benzodiazepines and Other Central Nervous System (CNS) Depressants
Clinical Impact: | Due to additive pharmacologic effect, the concomitant use of benzodiazepines or other CNS depressants, including alcohol, can increase the risk of hypotension, respiratory depression, profound sedation, coma, and death.
Intervention: | Reserve concomitant prescribing of these drugs for use in patients for whom alternative treatment options are inadequate. Limit dosages and durations to the minimum required. Inform patients and caregivers of this potential interaction and educate them on the signs and symptoms of respiratory depression (including sedation). If concomitant use is warranted, consider recommending or prescribing an opioid overdose reversal agent [see Dosage and Administration (2.2), Warnings and Precautions (5.1, 5.2, 5.3)].
Examples: | Benzodiazepines and other sedatives/hypnotics, anxiolytics, tranquilizers, muscle relaxants, general anesthetics, antipsychotics, gabapentinoids (gabapentin or pregabalin), other opioids, alcohol.
Serotonergic Drugs
Clinical Impact: | The concomitant use of opioids with other drugs that affect the serotonergic neurotransmitter system has resulted in serotonin syndrome.
Intervention: | If concomitant use is warranted, frequently evaluate the patient, particularly during treatment initiation and dose adjustment. Discontinue Codeine Sulfate Tablets if serotonin syndrome is suspected.
Examples: | Selective serotonin reuptake inhibitors (SSRIs), serotonin and norepinephrine reuptake inhibitors (SNRIs), tricyclic antidepressants (TCAs), triptans, 5-HT3 receptor antagonists, drugs that effect the serotonin neurotransmitter system (e.g., mirtazapine, trazodone, tramadol), certain muscle relaxants (i.e., cyclobenzaprine, metaxalone), monoamine oxidase (MAO) inhibitors (those intended to treat psychiatric disorders and also others, such as linezolid and intravenous methylene blue).
Monoamine Oxidase Inhibitors (MAOIs)
Clinical Impact: | MAOI interactions with opioids may manifest as serotonin syndrome or opioid toxicity (e.g., respiratory depression, coma) [see Warnings and Precautions (5.10)].
Intervention: | Do not use Codeine Sulfate Tablets in patients taking MAOIs or within 14 days of stopping such treatment.; If urgent use of an opioid is necessary, use test doses and frequent titration of small doses of other opioids (such as oxycodone, hydrocodone, oxymorphone, hydrocodone, or buprenorphine) to treat pain while closely monitoring blood pressure and signs and symptoms of CNS and respiratory depression.
Examples: | Phenelzine, tranylcypromine, linezolid.
Mixed Agonist/Antagonist and Partial Agonist Opioid Analgesics
Clinical Impact: | May reduce the analgesic effect of Codeine Sulfate Tablets and/or precipitate withdrawal symptoms.
Intervention: | Avoid concomitant use.
Examples: | Butorphanol, nalbuphine, pentazocine, buprenorphine.
Muscle Relaxants
Clinical Impact: | Codeine may enhance the neuromuscular blocking action of skeletal muscle relaxants and produce an increased degree of respiratory depression.
Intervention: | Because respiratory depression may be greater than otherwise expected, decrease the dosage of Codeine Sulfate Tablets and/or the muscle relaxant as necessary. Due to the risk of respiratory depression with concomitant use of skeletal muscle relaxants and opioids, consider recommending or prescribing an opioid overdose reversal agent [see Dosage and Administration (2.2), Warnings and Precautions (5.2, 5.3)].
Examples: | Cyclobenzaprine, metaxalone.
Diuretics
Clinical Impact: | Opioids can reduce the efficacy of diuretics by inducing the release of antidiuretic hormone.
Intervention: | Evaluate patients for signs of diminished diuresis and/or effects on blood pressure and increase the dosage of the diuretic as needed.
Anticholinergic Drugs
Clinical Impact: | The concomitant use of anticholinergic drugs may increase risk of urinary retention and/or severe constipation, which may lead to paralytic ileus.
Intervention: | Evaluate patients for signs of urinary retention or reduced gastric motility when Codeine Sulfate Tablets are used concomitantly with anticholinergic drugs.

8 USE IN SPECIFIC POPULATIONS

8.1 Pregnancy

Risk Summary:

Use of opioid analgesics for an extended period of time during pregnancy may cause neonatal opioid withdrawal syndrome [see Warnings and Precautions (5.4)]. Available data with Codeine Sulfate Tablets are insufficient to inform a drug-associated risk for major birth defects and miscarriage. In animal reproduction studies, codeine administration during organogenesis has been shown to produce delayed ossification in the offspring of mice at 1.4 times maximum recommended human dose (MRHD) of 360 mg/day, embryolethal and fetotoxic effects in the offspring of rats and hamsters at approximately 2 to 3 times the MRHD, and cranial malformations/cranioschisis in the offspring of hamsters between 2 and 8 times the MRHD [see Data].

All pregnancies have a background risk of birth defect, loss, or other adverse outcomes. In the U.S. general population, the estimated background risk of major birth defects and miscarriage in clinically recognized pregnancies is 2% to 4% and 15% to 20%, respectively.

Clinical Considerations:

Fetal/Neonatal Adverse Reactions: Use of opioid analgesics for an extended period of time during pregnancy for medical or nonmedical purposes can result in physical dependence in the neonate and neonatal opioid withdrawal syndrome shortly after birth.

Neonatal opioid withdrawal syndrome presents as irritability, hyperactivity and abnormal sleep pattern, high pitched cry, tremor, vomiting, diarrhea, and failure to gain weight. The onset, duration, and severity of neonatal opioid withdrawal syndrome vary based on the specific opioid used, duration of use, timing and amount of last maternal use, and rate of elimination of the drug by the newborn. Observe newborns for symptoms of neonatal opioid withdrawal syndrome and manage accordingly [see Warnings and Precautions (5.4)].

Labor or Delivery: Opioids cross the placenta and may produce respiratory depression and psycho-physiologic effects in neonates. An opioid overdose reversal agent, such as naloxone or nalmefene, must be available for reversal of opioid-induced respiratory depression in the neonate. Codeine Sulfate Tablets are not recommended for use in pregnant women during or immediately prior to labor, when other analgesic techniques are more appropriate. Opioid analgesics, including Codeine Sulfate Tablets, can prolong labor through actions which temporarily reduce the strength, duration, and frequency of uterine contractions. However, this effect is not consistent and may be offset by an increased rate of cervical dilation, which tends to shorten labor. Monitor neonates exposed to opioid analgesics during labor for signs of excess sedation and respiratory depression.

Data:

Animal Data: Studies on the reproductive and developmental effects of codeine have been reported in the published literature in hamsters, rats, mice and rabbits.

In a study in which pregnant hamsters were administered 150 mg/kg twice daily of codeine (oral; approximately 7 times the maximum recommended daily dose of 360 mg/day for adults on a mg/m^2 basis) during organogenesis cranial malformations (i.e., meningoencephalocele) in several fetuses were reported; as well as the observation of increases in the percentage of resorptions per litter. Doses of 50 and 150 mg/kg, bid resulted in fetotoxicity as demonstrated by decreased fetal body weight. In an earlier study in hamsters, single oral doses of 73 to 360 mg/kg level on Gestation Day 8 (oral; approximately 2 to 8 times the maximum recommended daily dose of 360 mg/day for adults on a mg/m^2 basis), reportedly produced cranioschisis in all of the fetuses examined.

In studies in rats, doses at the 120 mg/kg level (oral; approximately 3 times the maximum recommended daily dose of 360 mg/day for adults on a mg/m^2 basis) during organogenesis, in the toxic range for the adult animal, were associated with an increase in embryo resorption at the time of implantation.

In pregnant mice, a single 100 mg/kg dose (subcutaneous; approximately 1.4 times the recommended daily dose of 360 mg/day for adults on a mg/mg^2 basis) administered between Gestation Day 7 and 12 reportedly resulted in delayed ossification in the offspring.

No teratogenic effects were observed in rabbits administered up to 30 mg/kg (approximately 2 times the maximum recommended daily dose of 360 mg/day for adults on a mg/m^2 basis) of codeine during organogenesis.

Codeine (30 mg/kg) administered subcutaneously to pregnant rats during pregnancy and for 25 days after delivery increased neonatal mortality at birth. This dose is 0.8 times the maximum recommended human dose of 360 mg/day on a body surface area comparison.

8.2 Lactation

Risk Summary:

Codeine and its active metabolite, morphine, are present in human milk. There are published studies and cases that have reported excessive sedation, respiratory depression, and death in infants exposed to codeine via breast milk. Women who are ultra-rapid metabolizers of codeine achieve higher than expected serum levels of morphine, potentially leading to higher levels of morphine in breast milk that can be dangerous in their breastfed infants. In women with normal codeine metabolism (normal CYP2D6 activity), the amount of codeine secreted into human milk is low and dose-dependent.

There is no information on the effects of codeine on milk production. Because of the potential for serious adverse reactions, including excess sedation, respiratory depression, and death in a breastfed infant, advise patients that breastfeeding is not recommended during treatment with Codeine Sulfate Tablets [see Warnings and Precautions (5.4)].

Clinical Considerations:

If infants are exposed to Codeine Sulfate Tablets through breast milk, they should be monitored for excess sedation and respiratory depression. Withdrawal symptoms can occur in breastfed infants when maternal administration of an opioid analgesic is stopped, or when breastfeeding is stopped.

8.3 Females and Males of Reproductive Potential

Infertility:

Use of opioids for an extended period of time may cause reduced fertility in females and males of reproductive potential. It is not known whether these effects on fertility are reversible [see Adverse Reactions (6)].

8.4 Pediatric Use

The safety and effectiveness of Codeine Sulfate Tablets in pediatric patients have not been established.

Life-threatening respiratory depression and death have occurred in children who received codeine [see Warnings and Precautions (5.6)]. In most of the reported cases, these events followed tonsillectomy and/or adenoidectomy, and many of the children had evidence of being ultra-rapid metabolizers of codeine (i.e., multiple copies of the gene for cytochrome P450 isoenzyme 2D6 or high morphine concentrations). Children with sleep apnea may be particularly sensitive to the respiratory depressant effects of codeine. Because of the risk of life-threatening respiratory depression and death:

- Codeine Sulfate Tablets are contraindicated for all children younger than 12 years of age [see Contraindications (4)].
- Codeine Sulfate Tablets are contraindicated for post-operative management in pediatric patients younger than 18 years of age following tonsillectomy and/or adenoidectomy [see Contraindications (4)].
- Avoid the use of Codeine Sulfate Tablets in adolescents 12 to 18 years of age who have other risk factors that may increase their sensitivity to the respiratory depressant effects of codeine unless the benefits outweigh the risks. Risk factors include conditions associated with hypoventilation, such as postoperative status, obstructive sleep apnea, obesity, severe pulmonary disease, neuromuscular disease, and concomitant use of other medications that cause respiratory depression [see Warnings and Precautions (5.6)].

8.5 Geriatric Use

Elderly patients (aged 65 years or older) may have increased sensitivity to codeine. In general, use caution when selecting a dosage for an elderly patient, usually starting at the low end of the dosing range, reflecting the greater frequency of decreased hepatic, renal, or cardiac function and of concomitant disease or other drug therapy.

Respiratory depression is the chief risk for elderly patients treated with opioids, and has occurred after large initial doses were administered to patients who were not opioid-tolerant or when opioids were co-administered with other agents that depress respiration. Titrate the dosage of Codeine Sulfate Tablets slowly in geriatric patients and frequently reevaluate the patient for signs of central nervous system and respiratory depression [see Warnings and Precautions (5.9)].

Codeine is known to be substantially excreted by the kidney, and the risk of adverse reactions to this drug may be greater in patients with impaired renal function. Because elderly patients are more likely to have decreased renal function, care should be taken in dose selection, and it may be useful to regularly evaluate renal function.

8.6 Hepatic Impairment

No formal studies have been conducted in patients with hepatic impairment so the pharmacokinetics of codeine in this patient population are unknown. Start these patients with a lower than normal dosage of Codeine Sulfate Tablets or with longer dosing intervals and titrate slowly while regularly evaluating for signs of respiratory depression, sedation, and hypotension.

8.7 Renal Impairment

Codeine pharmacokinetics may be altered in patients with renal failure. Clearance may be decreased and the metabolites may accumulate to much higher plasma levels in patients with renal failure as compared to patients with normal renal function. Start these patients with a lower than normal dosage of Codeine Sulfate Tablets or with longer dosing intervals and titrate slowly while regularly evaluating for signs of respiratory depression, sedation, and hypotension.

9 DRUG ABUSE AND DEPENDENCE

9.1 Controlled Substance

Codeine Sulfate Tablets contain codeine, a Schedule II controlled substance.

9.2 Abuse

Codeine Sulfate Tablets contains codeine, a substance with high potential for misuse and abuse, which can lead to the development of substance use disorder, including addiction [see Warnings and Precautions (5.1)].

Misuse is the intentional use, for therapeutic purposes, of a drug by an individual in a way other than prescribed by a healthcare provider or for whom it was not prescribed.

Abuse is the intentional, non-therapeutic use of a drug, even once, for its desirable psychological or physiological effects.

Drug addiction is a cluster of behavioral, cognitive, and physiological phenomena that may include a strong desire to take the drug, difficulties in controlling drug use (e.g., continuing drug use despite harmful consequences, giving a higher priority to drug use than other activities and obligations), and possible tolerance or physical dependence.

Misuse and abuse of Codeine Sulfate Tablets increases risk of overdosage, which may lead to central nervous system and respiratory depression, hypotension, seizures, and death. The risk is increased with concurrent abuse of Codeine Sulfate Tablets with alcohol and/or other CNS depressants. Abuse of and addiction to opioids in some individuals may not be accompanied by concurrent tolerance and symptoms of physical dependence. In addition, abuse of opioids can occur in the absence of addiction.

All patients treated with opioids require careful and frequent reevaluation for signs of misuse, abuse, and addiction, because use of opioid analgesic products carries the risk of addiction even under appropriate medical use. Patients at high risk of Codeine Sulfate Tablets abuse include those with a history of prolonged use of any opioid, including products containing codeine, those with a history of drug or alcohol abuse, or those who use Codeine Sulfate Tablets in combination with other abused drugs.

“Drug-seeking” behavior is very common in persons with substance use disorders. Drug-seeking tactics include emergency calls or visits near the end of office hours, refusal to undergo appropriate examination, testing, or referral, repeated “loss” of prescriptions, tampering with prescriptions, and reluctance to provide prior medical records or contact information for other treating healthcare provider(s). “Doctor shopping” (visiting multiple prescribers to obtain additional prescriptions) is common among people who abuse drugs and people with substance use disorder. Preoccupation with achieving adequate pain relief can be appropriate behavior in a patient with inadequate pain control.

Codeine Sulfate Tablets, like other opioids, can be diverted for nonmedical use into illicit channels of distribution. Careful record-keeping of prescribing information, including quantity, frequency, and renewal requests, as required by state and federal law, is strongly advised.

Proper assessment of the patient, proper prescribing practices, periodic reevaluation of therapy, and proper dispensing and storage are appropriate measures that help to limit abuse of opioid drugs.

Risks Specific to Abuse of Codeine Sulfate Tablets:

Abuse of Codeine Sulfate Tablets poses a risk of overdose and death. The risk is increased with concurrent use of Codeine Sulfate Tablets with alcohol and/or other CNS depressants.

Codeine Sulfate Tablets is approved for oral use only.

Parenteral drug abuse is commonly associated with transmission of infectious diseases such as hepatitis and HIV.

9.3 Dependence

Both tolerance and physical dependence can develop during use of opioid therapy.

Tolerance is a physiological state characterized by a reduced response to a drug after repeated administration (i.e., a higher dose of a drug is required to produce the same effect that was once obtained at a lower dose).

Physical dependence is a state that develops as a result of a physiological adaptation in response to repeated drug use, manifested by withdrawal signs and symptoms after abrupt discontinuation or a significant dose reduction of a drug.

Withdrawal may be precipitated through the administration of drugs with opioid antagonist activity (e.g., naloxone, nalmefene), mixed agonist/antagonist analgesics (e.g., pentazocine, butorphanol, nalbuphine), or partial agonists (e.g., buprenorphine). Physical dependence may not occur to a clinically significant degree until after several days to weeks of continued use.

Do not rapidly reduce or abruptly discontinue Codeine Sulfate Tablets in a patient physically dependent on opioids. Rapid tapering of Codeine Sulfate Tablets in a patient physically dependent on opioids may lead to serious withdrawal symptoms, uncontrolled pain, and suicide. Rapid discontinuation has also been associated with attempts to find other sources of opioid analgesics, which may be confused with drug-seeking for abuse.

When discontinuing Codeine Sulfate Tablets, gradually taper the dosage using a patient-specific plan that considers the following: the dose of Codeine Sulfate Tablets the patient has been taking, the duration of treatment, and the physical and psychological attributes of the patient. To improve the likelihood of a successful taper and minimize withdrawal symptoms, it is important that the opioid tapering schedule is agreed upon by the patient. In patients taking opioids for an extended period of time at high doses, ensure that a multimodal approach to pain management, including mental health support (if needed), is in place prior to initiating an opioid analgesic taper [see Dosage and Administration (2.5), Warnings and Precautions (5.16)].

Infants born to mothers physically dependent on opioids will also be physically dependent and may exhibit respiratory difficulties and withdrawal signs [see Use in Specific Populations (8.1)].

10 OVERDOSAGE

Clinical Presentation:

Acute overdose with codeine can be manifested by respiratory depression, somnolence progressing to stupor or coma, skeletal muscle flaccidity, cold and clammy skin, constricted pupils, and, in some cases, pulmonary edema, bradycardia, hypotension, hypoglycemia, partial or complete airway obstruction, atypical snoring, and death. Marked mydriasis rather than miosis may be seen with hypoxia in overdose situations [see Clinical Pharmacology (12.2)]. Toxic leukoencephalopathy has been reported after opioid overdose and can present hours, days, or weeks after apparent recovery from the initial intoxication.

Treatment of Overdose:

In case of overdose, priorities are the reestablishment of a patent and protected airway and institution of assisted or controlled ventilation, if needed. Employ other supportive measures (including oxygen and vasopressors) in the management of circulatory shock and pulmonary edema as indicated. Cardiac arrest or arrhythmias will require advanced life-support measures.

For clinically significant respiratory or circulatory depression secondary to opioid overdose, administer an opioid overdose reversal agent such as naloxone or nalmefene.

Because the duration of opioid reversal is expected to be less than the duration of action of codeine in Codeine Sulfate Tablets, carefully monitor the patient until spontaneous respiration is reliably reestablished. If the response to an opioid overdose reversal agent is suboptimal or only brief in nature, administer additional reversal agent as directed by the product’s prescribing information.

In an individual physically dependent on opioids, administration of the recommended usual dosage of the opioid overdose reversal agent will precipitate an acute withdrawal syndrome. The severity of the withdrawal symptoms experienced will depend on the degree of physical dependence and the dose of the reversal agent administered. If a decision is made to treat serious respiratory depression in the physically dependent patient, administration of the reversal agent should be begun with care and by titration with smaller than usual doses of the reversal agent.

11 DESCRIPTION

Codeine Sulfate Tablets, USP contain codeine, an opioid agonist, available for oral administration containing either 15 mg, 30 mg, or 60 mg of codeine sulfate, USP. The chemical name is morphinan-6-ol,7,8-didehydro-4,5-epoxy-3-methoxy-17-methyl-(5α,6α)-, sulfate (2:1) (salt), trihydrate. Its molecular formula is (C18H21NO3)2 • H2SO4 • 3H2O and its molecular weight is 750.85 g/mol.

Its structure is as follows:

Codeine sulfate trihydrate is a fine, white, crystalline powder which is soluble in water and insoluble in chloroform and ether.

The inactive ingredients in Codeine Sulfate Tablets, USP include: colloidal silicon dioxide, microcrystalline cellulose, pregelatinized starch and stearic acid.

12 CLINICAL PHARMACOLOGY

12.1 Mechanism of Action

Codeine sulfate is an opioid agonist relatively selective for the mu-opioid receptor, but with a much weaker affinity than morphine. The analgesic properties of codeine have been speculated to come from its conversion to morphine, although the exact mechanism of analgesic action remains unknown.

12.2 Pharmacodynamics

Effects on the Central Nervous System:

Codeine produces respiratory depression by direct action on brain stem respiratory centers. The respiratory depression involves a reduction in the responsiveness of the brain stem respiratory centers to both increases in carbon dioxide tension and electrical stimulation.

Codeine causes miosis, even in total darkness. Pinpoint pupils are a sign of opioid overdose but are not pathognomonic (e.g., pontine lesions of hemorrhagic or ischemic origins may produce similar findings). Marked mydriasis rather than miosis may be seen due to hypoxia in overdose situations.

Effects on the Gastrointestinal Tract and Other Smooth Muscle:

Codeine causes a reduction in motility associated with an increase in smooth muscle tone in the antrum of the stomach and duodenum. Digestion of food in the small intestine is delayed and propulsive contractions are decreased. Propulsive peristaltic waves in the colon are decreased, while tone may be increased to the point of spasm, resulting in constipation. Other opioid-induced effects may include a reduction in biliary and pancreatic secretions, spasm of sphincter of Oddi, transient elevations in serum amylase, and opioid-induced esophageal dysfunction (OIED).

Effects on the Cardiovascular System:

Codeine produces peripheral vasodilation which may result in orthostatic hypotension or syncope. Manifestations of histamine release and/or peripheral vasodilation may include pruritus, flushing, red eyes, sweating, and/or orthostatic hypotension.

Effects on the Endocrine System:

Opioids inhibit the secretion of adrenocorticotropic hormone (ACTH), cortisol, and luteinizing hormone (LH) in humans [see Adverse Reactions (6)]. They also stimulate prolactin, growth hormone (GH) secretion, and pancreatic secretion of insulin and glucagon. Use of opioids for an extended period of time may influence the hypothalamic-pituitary-gonadal axis, leading to androgen deficiency that may manifest as low libido, impotence, erectile dysfunction, amenorrhea, or infertility. The causal role of opioids in the clinical syndrome of hypogonadism is unknown because the various medical, physical, lifestyle, and psychological stressors that may influence gonadal hormone levels have not been adequately controlled for in studies conducted to date [see Adverse Reactions (6)].

Effects on the Immune System:

Opioids have been shown to have a variety of effects on components of the immune system in in vitro and animal models. The clinical significance of these findings is unknown. Overall, the effects of opioids appear to be modestly immunosuppressive.

Concentration–Efficacy Relationships:

The minimum effective analgesic concentration will vary widely among patients, especially among patients who have been previously treated with opioid agonists. The minimum effective analgesic concentration of codeine for any individual patient may increase over time due to an increase in pain, the development of a new pain syndrome, and/or the development of analgesic tolerance [see Dosage and Administration (2.1, 2.3)].

Concentration–Adverse Reaction Relationships:

There is a relationship between increasing codeine plasma concentration and increasing frequency of dose-related opioid adverse reactions such as nausea, vomiting, CNS effects, and respiratory depression. In opioid-tolerant patients, the situation may be altered by the development of tolerance to opioid-related adverse reactions [see Dosage and Administration (2.1, 2.3, 2.4)].

12.3 Pharmacokinetics

Absorption:

Codeine is absorbed from the gastrointestinal tract with maximum plasma concentration occurring 60 minutes post administration. Administration of 15 mg of codeine sulfate every four hours for 5 days resulted in steady-state concentrations of codeine, morphine, morphine-3-glucuronide (M3G) and morphine-6-glucuronide (M6G) within 48 hours.

Food Effect: When 60 mg codeine sulfate was administered 30 minutes after ingesting a high fat/high calorie meal, there was no significant change in the rate and extent of absorption of codeine.

Distribution:

Codeine has been reported to have an apparent volume of distribution of approximately 3 to 6 L/kg, indicating extensive distribution of the drug into tissues. Codeine has low plasma protein binding with about 7% to 25% of codeine bound to plasma proteins.

Elimination:

Codeine is metabolized by conjugation to codeine-6-glucuronide (70% to 80%), by O-demethylation to morphine (5% to 10%), and by N-demethylation to norcodeine (~10%). Approximately 90% of the total dose of codeine is excreted through the kidneys. The plasma half-lives of codeine and its metabolites have been reported to be approximately 3 hours.

Metabolism: About 70% to 80% of the administered dose of codeine is metabolized by conjugation with glucuronic acid to codeine-6-glucuronide (C6G) and via O-demethylation to morphine (about 5% to 10%) and N-demethylation to norcodeine (about 10%) respectively. UDP-glucuronosyltransferase (UGT) 2B7 and 2B4 are the major enzymes mediating glucuronidation of codeine to C6G. Cytochrome P450 2D6 is the major enzyme responsible for conversion of codeine to morphine and P450 3A4 is the major enzyme mediating conversion of codeine to norcodeine. Morphine and norcodeine are further metabolized by conjugation with glucuronic acid. The glucuronide metabolites of morphine are morphine-3-glucuronide (M3G) and morphine-6-glucuronide (M6G). Morphine and M6G are known to have analgesic activity in humans. The analgesic activity of C6G in humans is unknown. Norcodeine and M3G are generally not considered to possess analgesic properties.

Excretion: Approximately 90% of the total dose of codeine is excreted through the kidneys, of which approximately 10% is unchanged codeine. Plasma half-lives of codeine and its metabolites have been reported to be approximately 3 hours.

13 NONCLINICAL TOXICOLOGY

13.1 Carcinogenesis, Mutagenesis, Impairment of Fertility

Carcinogenesis:

Two-year carcinogenicity studies have been conducted in F344/N rats and B6C3F1 mice. There was no evidence of carcinogenicity in male and female rats, respectively, at dietary doses up to 70 and 80 mg/kg/day of codeine (approximately 2 times the maximum recommended daily dose of 360 mg/day for adults on a mg/m^2 basis) for two years. Similarly there was no evidence of carcinogenicity activity in male and female mice at dietary doses up to 400 mg/kg/day of codeine (approximately 5 times the maximum recommended daily dose of 360 mg/day for adults on a mg/m^2 basis) for two years.

Mutagenesis:

Codeine was not mutagenic in the in vitro bacterial reverse mutation assay or clastogenic in the in vitro Chinese hamster ovary cell chromosome aberration assay.

Impairment of Fertility:

No animal studies were conducted to evaluate the effect of codeine on male or female fertility.

16 HOW SUPPLIED/STORAGE AND HANDLING

Codeine Sulfate Tablets, USP

15 mg tablet: supplied as white to off-white biconvex tablets with “15” debossed on the scored side and “54 613” debossed on the other side.

NDC 0054-0243-24: 10 x 10 Unit-Dose

30 mg tablet: supplied as white to off-white biconvex tablets with “30” debossed on the scored side and “54 783” debossed on the other side.

NDC 0054-0244-24: 10 x 10 Unit-Dose

NDC 0054-0244-25: Bottle of 100 Tablets

60 mg tablet: supplied as white to off-white biconvex tablets with “60” debossed on the scored side and “54 412” debossed on the other side.

NDC 0054-0245-25: Bottle of 100 Tablets

Storage

Store at 20° to 25°C (68° to 77°F), excursions permitted between 15° to 30°C (59° to 86°F). [See USP Controlled Room Temperature.]

Protect from moisture.

Dispense in a tight, light-resistant container as defined in the USP/NF.

Blisters are not child-resistant. Use child-resistant closure if dispensing to outpatient.

Store Codeine Sulfate Tablets securely and dispose of properly.

17 PATIENT COUNSELING INFORMATION

Advise the patient to read the FDA-approved patient labeling (Medication Guide).

Storage and Disposal:

Because of the risks associated with accidental ingestion, misuse, and abuse, advise patients to store Codeine Sulfate Tablets securely, out of sight and reach of children, and in a location not accessible by others, including visitors to the home. Inform patients that leaving Codeine Sulfate Tablets unsecured can pose a deadly risk to others in the home [see Warnings and Precautions (5.1, 5.2), Drug Abuse and Dependence (9.2)].

Advise patients and caregivers that when medicines are no longer needed, they should be disposed of promptly. Inform patients that medicine take-back options are the preferred way to safely dispose of most types of unneeded medicines. If no take back programs or DEA-registered collectors are available, instruct patients to dispose of Codeine Sulfate Tablets by following these four steps:

- Mix Codeine Sulfate Tablets with an unpalatable substance such as dirt, cat litter, or used coffee grounds;
- Place the mixture in a container such as a sealed plastic bag;
- Throw the container in the household trash;
- Remove all personal information on the prescription label of the empty bottle

Inform patients that they can visit www.fda.gov/drugdisposal for additional information on disposal of unused medicines.

Addiction, Abuse, and Misuse:

Inform patients that the use of Codeine Sulfate Tablets, even when taken as recommended, can result in addiction, abuse, and misuse, which can lead to overdose and death [see Warnings and Precautions (5.1)]. Instruct patients not to share Codeine Sulfate Tablets with others and to take steps to protect Codeine Sulfate Tablets from theft or misuse.

Life-Threatening Respiratory Depression:

Inform patients of the risk of life-threatening respiratory depression, including information that the risk is greatest when starting Codeine Sulfate Tablets or when the dosage is increased, and that it can occur even at recommended dosages.

Educate patients and caregivers on how to recognize respiratory depression and emphasize the importance of calling 911 or getting emergency medical help right away in the event of a known or suspected overdose [see Warnings and Precautions (5.2)].

Accidental Ingestion:

Inform patients that accidental ingestion, especially by children, may result in respiratory depression or death [see Warnings and Precautions (5.2)].

Interactions with Benzodiazepines and Other CNS Depressants:

Inform patients and caregivers that potentially fatal additive effects may occur if Codeine Sulfate Tablets are used with benzodiazepines or other CNS depressants, including alcohol (e.g., non-benzodiazepine sedative/hypnotics, anxiolytics, tranquilizers, muscle relaxants, general anesthetics, antipsychotics, gabapentinoids [gabapentin or pregabalin], and other opioids), and not to use these concomitantly unless supervised by a healthcare provider [see Warnings and Precautions (5.3), Drug Interactions (7)].

Patient Access to an Opioid Overdose Reversal Agent for the Emergency Treatment of Opioid Overdose:

Inform patients and caregivers about opioid overdose reversal agents (e.g., naloxone, nalmefene). Discuss the importance of having access to an opioid overdose reversal agent, especially if the patient has risk factors for overdose (e.g., concomitant use of CNS depressants, a history of opioid use disorder, or prior opioid overdose) or if there are household members (including children) or other close contacts at risk for accidental ingestion or opioid overdose.

Discuss with the patient the options for obtaining an opioid overdose reversal agent (e.g., prescription, over-the-counter, or as part of a community-based program) [see Dosage and Administration (2.2), Warnings and Precautions (5.3)].

Educate patients and caregivers on how to recognize the signs and symptoms of an overdose.

Explain to patients and caregivers that effects of opioid overdose reversal agents like naloxone and nalmefene are temporary, and that they must call 911 or get emergency medical help right away in all cases of known or suspected opioid overdose, even if an opioid overdose reversal agent is administered [see Overdosage (10)].

Advise patients and caregivers:

- how to treat with the overdose reversal agent in the event of an opioid overdose.
- to tell family and friends about the opioid overdose reversal agent, and to keep it in a place where family and friends can access it in an emergency.
- to read the Patient Information (or other educational material) that will come with their opioid overdose reversal agent. Emphasize the importance of doing this before an opioid emergency happens, so the patient and caregiver will know what to do.

Ultra-Rapid Codeine Metabolism of Codeine and Other Risk Factors for Life-Threatening Respiratory Depression in Children:

Advise caregivers that Codeine Sulfate Tablets are contraindicated in all children younger than 12 years of age and in children younger than 18 years of age following tonsillectomy and/or adenoidectomy. Advise caregivers of children 12 to 18 years of age receiving Codeine Sulfate Tablets to monitor for signs of respiratory depression [see Warnings and Precautions (5.6)].

Hyperalgesia and Allodynia:

Inform patients and caregivers not to increase opioid dosage without first consulting a clinician. Advise patients to seek medical attention if they experience symptoms of hyperalgesia, including worsening pain, increased sensitivity to pain, or new pain [see Warnings and Precautions (5.8), Adverse Reactions (6)].

Serotonin Syndrome:

Inform patients that opioids could cause a rare but potentially life-threatening condition called serotonin syndrome resulting from concomitant administration of serotonergic drugs. Warn patients of the symptoms of serotonin syndrome and to seek medical attention right away if symptoms develop. Instruct patients to inform their physicians if they are taking, or plan to take serotonergic medications [see Drug Interactions (7)].

MAOI Interaction:

Inform patients not to take Codeine Sulfate Tablets while using any drugs that inhibit monoamine oxidase. Patients should not start MAOIs while taking Codeine Sulfate Tablets [see Warnings and Precautions (5.10), Drug Interactions (7)].

Important Administration Instructions:

Instruct patients how to properly take Codeine Sulfate Tablets.

- Advise patients not to adjust the dose of Codeine Sulfate Tablets without consulting a physician or other healthcare professional.

Important Discontinuation Instructions:

In order to avoid developing withdrawal symptoms, instruct patients not to discontinue Codeine Sulfate Tablets without first discussing a tapering plan with the prescriber [see Dosage and Administration (2.5)].

Driving or Operating Heavy Machinery:

Inform patients that Codeine Sulfate Tablets may impair the ability to perform potentially hazardous activities such as driving a car or operating heavy machinery. Advise patients not to perform such tasks until they know how they will react to the medication [see Warnings and Precautions (5.17)].

Constipation:

Advise patients of the potential for severe constipation, including management instructions and when to seek medical attention [see Adverse Reactions (6), Clinical Pharmacology (12.2)].

Adrenal Insufficiency:

Inform patients that opioids could cause adrenal insufficiency, a potentially life-threatening condition. Adrenal insufficiency may present with non-specific symptoms and signs such as nausea, vomiting, anorexia, fatigue, weakness, dizziness, and low blood pressure. Advise patients to seek medical attention if they experience a constellation of these symptoms [see Warnings and Precautions (5.11)].

Hypotension:

Inform patients that Codeine Sulfate Tablets may cause orthostatic hypotension and syncope. Instruct patients how to recognize symptoms of low blood pressure and how to reduce the risk of serious consequences should hypotension occur (e.g., sit or lie down, carefully rise from a sitting or lying position) [see Warnings and Precautions (5.12)].

Anaphylaxis:

Inform patients that anaphylaxis has been reported with ingredients contained in Codeine Sulfate Tablets. Advise patients how to recognize such a reaction and when to seek medical attention [see Contraindications (4), Adverse Reactions (6)].

Pregnancy:

Neonatal Opioid Withdrawal Syndrome: Inform female patients of reproductive potential that use of Codeine Sulfate Tablets for an extended period of time during pregnancy can result in neonatal opioid withdrawal syndrome, which may be life-threatening if not recognized and treated [see Warnings and Precautions (5.4), Use in Specific Populations (8.1)].

Embryo-Fetal Toxicity: Inform female patients of reproductive potential that Codeine Sulfate Tablets can cause fetal harm and to inform the healthcare provider of a known or suspected pregnancy [see Use in Specific Populations (8.1)].

Lactation:

Advise women that breastfeeding is not recommended during treatment with Codeine Sulfate Tablets [see Use in Specific Populations (8.2)].

Infertility:

Inform patients that use of opioids for an extended period of time may cause reduced fertility. It is not known whether these effects on fertility are reversible [see Use in Specific Populations (8.3)].

Distributed by:
Hikma Pharmaceuticals USA Inc.
Berkeley Heights, NJ 07922
C50000445/03

Medication Guide

Codeine Sulfate (koe’ deen sul’ fate) Tablets, USP CII

Codeine Sulfate Tablets are:

- A strong prescription pain medicine that contains an opioid (narcotic) that is used to manage mild to moderate pain, where treatment with an opioid is appropriate, and when other pain treatments such as non-opioid pain medicines do not treat your pain well enough or you cannot tolerate them.
- An opioid pain medicine that can put you at risk for overdose and death. Even if you take your dose correctly as prescribed you are at risk for opioid addiction, abuse, and misuse that can lead to death.

Important information about Codeine Sulfate Tablets:

- Get emergency help or call 911 right away if you take too much Codeine Sulfate Tablets (overdose). When you first start taking Codeine Sulfate Tablets, when your dose is changed, or if you take too much (overdose), serious or life-threatening breathing problems that can lead to death may occur. Ask your healthcare provider about medicines like naloxone or nalmefene that can be used in an emergency to reverse an opioid overdose.
- Taking Codeine Sulfate Tablets with other opioid medicines, benzodiazepines, gabapentinoids (gabapentin or pregabalin), alcohol, or other central nervous system depressants (including street drugs) can cause severe drowsiness, decreased awareness, breathing problems, coma, and death.
- Never give anyone else your Codeine Sulfate Tablets. They could die from taking it. Selling or giving away Codeine Sulfate Tablets is against the law.
- Store Codeine Sulfate Tablets securely, out of sight and reach of children, and in a location not accessible by others, including visitors to the home.

Important Information Guiding Use in Pediatric Patients:

- Do not give Codeine Sulfate Tablets to a child younger than 12 years of age.
- Do not give Codeine Sulfate Tablets to a child younger than 18 years of age after surgery to remove the tonsils and/or adenoids.
- Avoid giving Codeine Sulfate Tablets to children between 12 to 18 years of age who have risk factors for breathing problems such as obstructive sleep apnea, obesity, or underlying lung problems.

Do not take Codeine Sulfate Tablets if you have:

- Severe asthma, trouble breathing, or other lung problems.
- A bowel blockage or have narrowing of the stomach or intestines.
- An allergy to Codeine Sulfate Tablets or any of the ingredients.

Before taking Codeine Sulfate Tablets, tell your healthcare provider if you have a history of:

- Head injury, seizures
- Problems urinating
- Abuse of street or prescription drugs, alcohol addiction, opioid overdose, or mental health problems.

- Liver, kidney, thyroid problems
- Pancreas or gallbladder problems
- Have been told by your healthcare provider that you are a “rapid metabolizer” of certain medicines

Tell your healthcare provider if you are:

- noticing your pain getting worse. If your pain gets worse after you take Codeine Sulfate Tablets, do not take more of Codeine Sulfate Tablets without first talking to your healthcare provider. Talk to your healthcare provider if the pain that you have increases, if you feel more sensitive to pain, or if you have new pain after taking Codeine Sulfate Tablets.
- pregnant or planning to become pregnant. Use of Codeine Sulfate Tablets for an extended period of time during pregnancy can cause withdrawal symptoms in your newborn baby that could be life-threatening if not recognized and treated.
- breastfeeding. Not recommended; may harm your baby.
- living in a household where there are small children or someone who has abused street or prescription drugs.
- taking prescription or over-the-counter medicines, vitamins, or herbal supplements. Taking codeine sulfate with certain other medicines can cause serious side effects that could lead to death.

When taking Codeine Sulfate Tablets:

- Do not change your dose. Take Codeine Sulfate Tablets exactly as prescribed by your healthcare provider. Use the lowest dose possible for the shortest time needed.
- For acute (short-term) pain, you may only need to take Codeine Sulfate Tablets for a few days. You may have some Codeine Sulfate Tablets left over that you did not use. See disposal information at the bottom of this section for directions on how to safely throw away (dispose of) your unused Codeine Sulfate Tablets.
- Take your prescribed dose every 4 hours as needed for pain. Do not take more than your prescribed dose. If you miss a dose, take your next dose at your usual time.
- Call your healthcare provider if the dose you are taking does not control your pain.
- If you have been taking Codeine Sulfate Tablets regularly, do not stop taking codeine sulfate without talking to your healthcare provider.
- Dispose of expired, unwanted, or unused Codeine Sulfate Tablets by taking your drug to an authorized DEA-registered collector or drug take-back program. If one is not available, you can dispose of Codeine Sulfate Tablets by mixing the product with dirt, cat litter, or coffee grounds; placing the mixture in a sealed plastic bag and throwing the bag in your trash. Visit www.fda.gov/drugdisposal for additional information on disposal of unused medicines.

While taking Codeine Sulfate Tablets DO NOT:

- Drive or operate heavy machinery, until you know how codeine sulfate affects you. Codeine sulfate can make you sleepy, dizzy, or lightheaded.
- Drink alcohol or use prescription or over-the-counter medicines that contain alcohol. Using products containing alcohol during treatment with codeine sulfate may cause you to overdose and die.

The possible side effects of Codeine Sulfate Tablets:

- Constipation, nausea, sleepiness, vomiting, tiredness, headache, dizziness, abdominal pain. Call your healthcare provider if you have any of these symptoms and they are severe.

Get emergency medical help or call 911 right away if you have:

- Trouble breathing, shortness of breath, fast heartbeat, chest pain, swelling of your face, tongue, or throat, extreme drowsiness, light-headedness when changing positions, feeling faint, agitation, high body temperature, trouble walking, stiff muscles, or mental changes such as confusion.
- If you are a nursing mother taking Codeine Sulfate Tablets and your breastfeeding baby has increased sleepiness, confusion, difficulty breathing, shallow breathing, limpness, or difficulty breastfeeding.

These are not all the possible side effects of codeine sulfate. Call your healthcare provider for medical advice about side effects. You may report side effects to FDA at 1-800-FDA-1088. For more information go to dailymed.nlm.nih.gov

Distributed by:
Hikma Pharmaceuticals USA Inc.
Berkeley Heights, NJ 07922
For more information, please call Hikma Pharmaceuticals at 1-800-962-8364.

This Medication Guide has been approved by the U.S. Food and Drug Administration

C50000445/03
Revised December 2025

PACKAGE/LABEL – 15 mg Tablet, Unit-Dose Carton

NDC 0054-0243-24
10x10 Unit-Dose Tablets

Codeine Sulfate
Tablets, USP CII
15 mg
Rx only

PACKAGE/LABEL – 30 mg Bottle Label

NDC 0054-0244-25
100 Tablets

Codeine Sulfate
Tablets, USP CII
30 mg
Rx only

PACKAGE/LABEL – 60 mg Bottle Label

NDC 0054-0245-25
100 Tablets

Codeine Sulfate
Tablets, USP CII
60 mg
Rx only